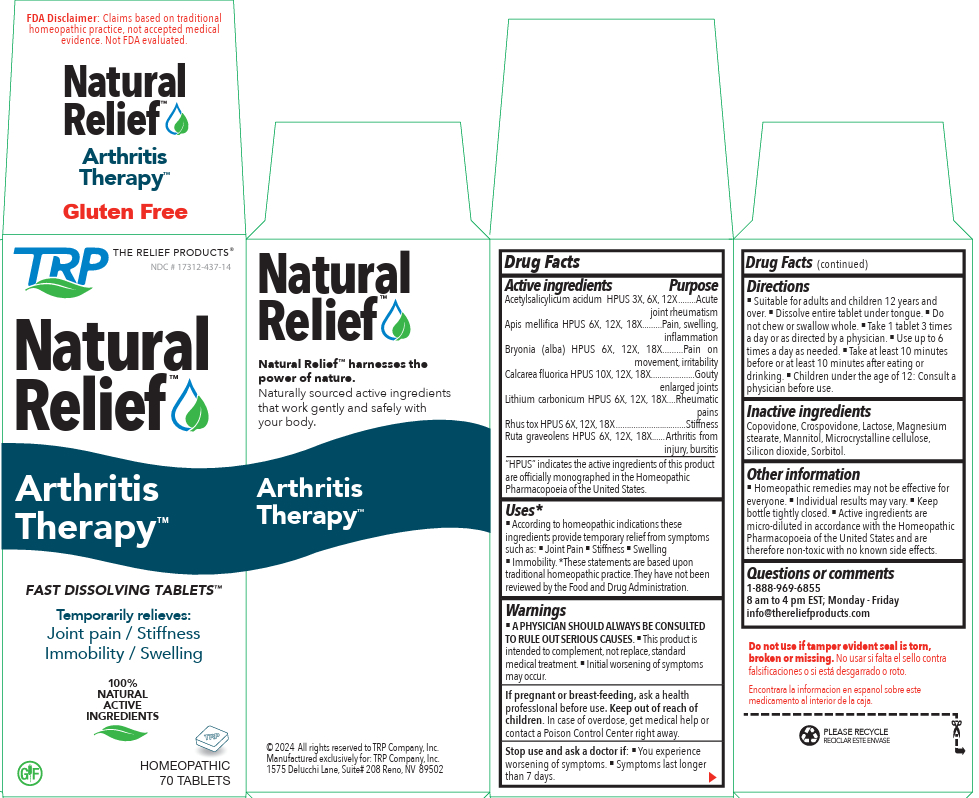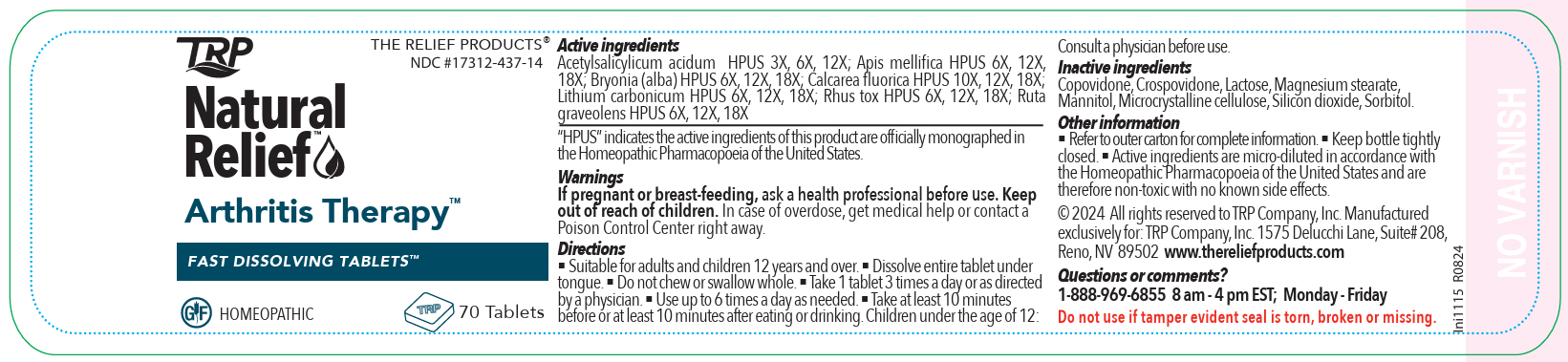 DRUG LABEL: Natural Relief Arthritis Therapy
NDC: 17312-437 | Form: TABLET, ORALLY DISINTEGRATING
Manufacturer: TRP Company
Category: homeopathic | Type: HUMAN OTC DRUG LABEL
Date: 20251112

ACTIVE INGREDIENTS: APIS MELLIFERA 6 [hp_X]/1 1; BRYONIA ALBA ROOT 6 [hp_X]/1 1; CALCIUM FLUORIDE 10 [hp_X]/1 1; LITHIUM CARBONATE 6 [hp_X]/1 1; TOXICODENDRON PUBESCENS LEAF 6 [hp_X]/1 1; RUTA GRAVEOLENS FLOWERING TOP 6 [hp_X]/1 1; SALICYLIC ACID 3 [hp_X]/1 1
INACTIVE INGREDIENTS: MANNITOL; SORBITOL; CROSPOVIDONE; CELLULOSE, MICROCRYSTALLINE; COPOVIDONE; SILICON DIOXIDE; LACTOSE; MAGNESIUM STEARATE

Natural Relief Arthritis Therapy

Active ingredients

Acetylsalicylicum acidum 3X, 6X, 12X

Apis mellifica 6X, 12X, 18X

Bryonia (alba) 6X, 12X, 18X

Calcarea fluorica 10X, 12X, 18X

Lithium carbonicum 6X, 12X, 18X

Rhus tox 6X, 12X, 18X

Ruta graveolens 6X, 12X, 18X

Purpose

Acetylsalicylicum acidum - Acute joint rheumatism

Apis mellifica -Pain, swelling, inflammation

Bryonia (alba) - Pain on movement, irritability

Calcarea fluorica - Gouty enlarged joints

Lithium carbonicum - Rheumatic pains

Rhus tox - Stiffness

Ruta graveolens - Arthritis from injury, bursitis

Uses*

According to homeopathic indications these ingredients provide temporary relief from symptoms such as:

- Joint Pain
- Stiffness
- Swelling
- Immobility.

*These statements are based upon traditional homeopathic practice. They have not been reviewed by the Food and Drug Administration.

Warnings

A PHYSICIAN SHOULD ALWAYS BE CONSULTED TO RULE OUT SERIOUS CAUSES.

- This product is intended to complement, not replace, standard medical treatment.
- Initial worsening of symptoms may occur.

PREGNANCY OR BREAST FEEDING

If pregnant or breast-feeding, ask a health professional before use.

Keep out of reach of children. In case of overdose, get medical help or contact a Poison Control Center right away.

Stop use and ask a doctor if:

- You experience worsening of symptoms.
- Symptoms last longer than 7 days.

Directions

- Suitable for adults and children 12 years and over.
- Dissolve entire tablet under tongue.
- Do not chew or swallow whole.
- Take 1 tablet 3 times a day or as directed by a physician.
- Use up to 6 times a day as needed.
- Take at least 10 minutes before or at least 10 minutes after eating or drinking.
- Children under the age of 12: Consult a physician before use.

Inactive ingredients

Copovidone, Crospovidone, Lactose, Magnesium stearate, Mannitol, Microcrystalline cellulose, Silicon dioxide, Sorbitol.

Other information

- Homeopathic remedies may not be effective for everyone.
- Individual results may vary.
- Keep bottle tightly closed.
- Active ingredients are micro-diluted in accordance with the Homeopathic Pharmacopoeia of the United States and are therefore non-toxic with no known side effects.

Questions or comments

1-888-969-6855 8 am to 4 pm EST; Monday - Friday info@thereliefproducts.com